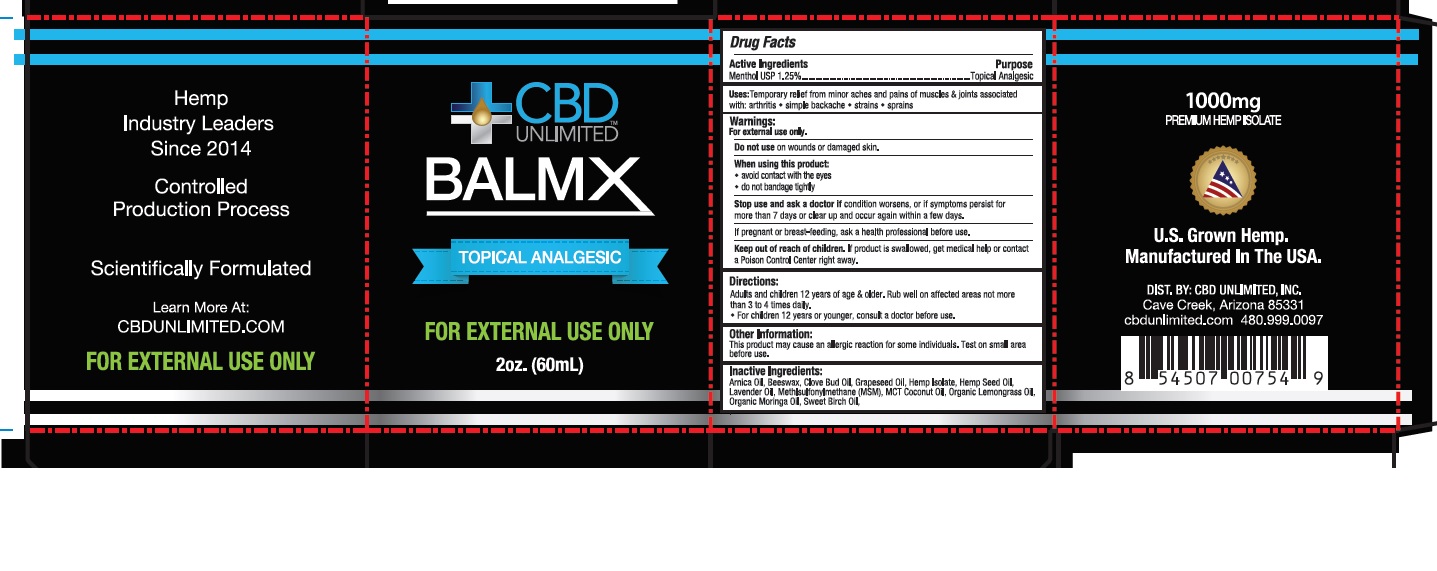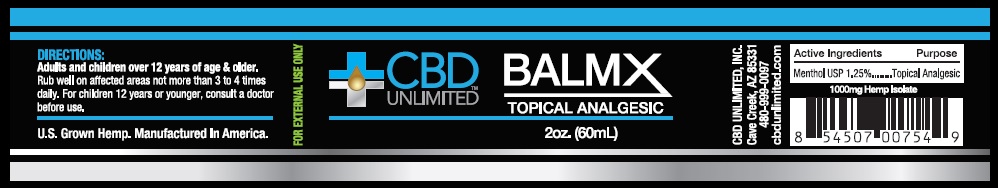 DRUG LABEL: CBD UNLIMITED BALMX TOPICAL ANALGESIC
NDC: 73045-001 | Form: CREAM
Manufacturer: ENDEXX CORPORATION
Category: otc | Type: HUMAN OTC DRUG LABEL
Date: 20210125

ACTIVE INGREDIENTS: MENTHOL 1.25 g/100 mL
INACTIVE INGREDIENTS: ARNICA MONTANA FLOWER; YELLOW WAX; HEMP; CLOVE OIL; COCONUT OIL; GRAPE SEED OIL; CANNABIS SATIVA SEED OIL; LAVENDER OIL; WEST INDIAN LEMONGRASS OIL; DIMETHYL SULFONE; MORINGA OLEIFERA SEED OIL; METHYL SALICYLATE

CBD UNLIMITED BALMX TOPICAL ANALGESIC

Active ingredient

Menthol 1.25%

Purpose

Topical Analgesic

Inactive ingredients

Arnica Oil, Beeswax, Clove Bud Oil, Grapeseed Oil, Hemp Isolate, Hemp Seed Oil, Lavender Oil, MSM (Methylsulfonylmethane), MCT Coconut Oil, Organic Lemongrass Oil, Organic Moringa Oil, Sweet Birch Oil.

Uses

Temporary relief from minor aches and pains of muscles & joints associated with: arthritis, simple backache, strains, sprains

Warnings:

For external use only.

Do not use on wounds or damaged skin.

When using this product: Avoid contact with the eyes. Do not bandage tightly.

Stop use and ask a doctor ifcondition worsens, or if symptoms persist for more than 7 days or clear up and occur again within a few days.

If pregnant or breast-feeding ask a health professional before use.

Keep Out of Reach of Children

If product is swallowed get medical help or contact a Poison Control Center right away.

Directions:

Adults and children 12 years of age & older. Rub well on affected area not more than 3 to 4 times daily. For children 12 years or younger, consult a doctor before use.

Distributed By:

CBD UNLIMITED INC

Principal Display Panel

CBD UNLIMITED BALMX

TOPICAL ANALGESIC

2 fl. oz. (60mL) Balm